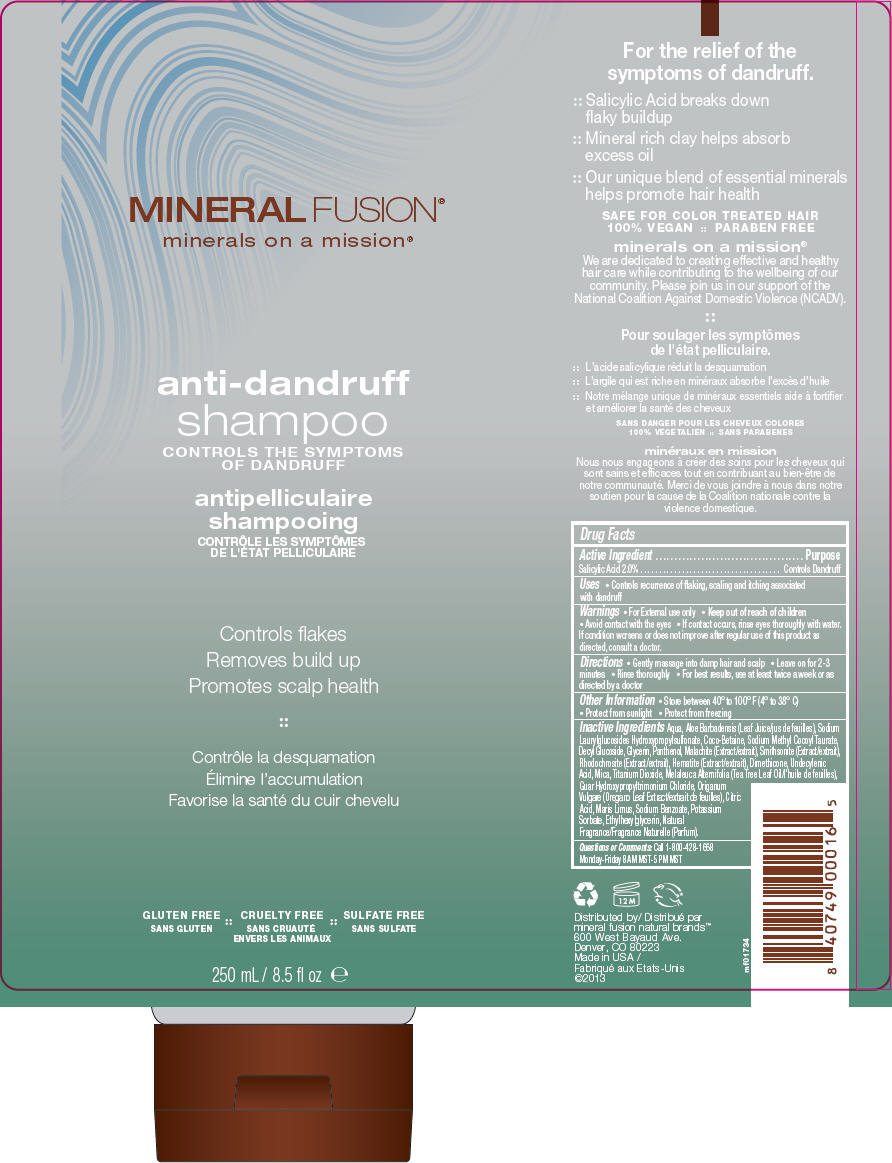 DRUG LABEL: Anti-Dandruff
NDC: 55789-1734 | Form: SHAMPOO
Manufacturer: Mineral Fusion Natural Brands
Category: otc | Type: HUMAN OTC DRUG LABEL
Date: 20190917

ACTIVE INGREDIENTS: SALICYLIC ACID 20 mg/1 mL
INACTIVE INGREDIENTS: WATER; ALOE VERA LEAF; SODIUM LAUROYL HYDROXYPROPYL SULFONATE; COCO-BETAINE; SODIUM METHYL COCOYL TAURATE; DECYL GLUCOSIDE; GLYCERIN; PANTHENOL; CUPRIC CARBONATE; ZINC CARBONATE; MANGANESE CARBONATE; FERRIC OXIDE RED; DIMETHICONE; UNDECYLENIC ACID; MICA; TITANIUM DIOXIDE; TEA TREE OIL; GUAR HYDROXYPROPYLTRIMONIUM CHLORIDE (1.7 SUBSTITUENTS PER SACCHARIDE); OREGANO; CITRIC ACID MONOHYDRATE; SODIUM BENZOATE; POTASSIUM SORBATE; ETHYLHEXYLGLYCERIN

Anti-Dandruff Shampoo

Drug Facts

Active Ingredient

Salicylic Acid 2.0%

Purpose

Controls Dandruff

Uses

- Controls recurrence of flaking, scaling and itching associated with dandruff

Warnings

- For External use only

- Keep out of reach of children

WHEN USING

- Avoid contact with the eyes

ASK DOCTOR

- If contact occurs, rinse eyes thoroughly with water. If condition worsens or does not improve after regular use of this product as directed, consult a doctor.

Directions

- Gently massage into damp hair and scalp
- Leave on for 2-3 minutes
- Rinse thoroughly
- For best results, use at least twice a week or as directed by a doctor

Other Information

- Store between 40° to 100° F (4° to 38° C)
- Protect from sunlight
- Protect from freezing

Inactive Ingredients

Aqua, Aloe Barbadensis (Leaf Juice/jus de feuilles), Sodium Laurylglucosides Hydroxypropylsulfonate, Coco-Betaine, Sodium Methyl Cocoyl Taurate, Decyl Glucoside, Glycerin, Panthenol, Malachite (Extract/extrait), Smithsonite (Extract/extrait), Rhodochrosite (Extract/extrait), Hematite (Extract/extrait), Dimethicone, Undecylenic Acid, Mica, Titanium Dioxide, Melaleuca Alternifolia (Tea Tree Leaf Oil/l'huile de feuilles), Guar Hydroxypropyltrimonium Chloride, Origanum Vulgare (Oregano Leaf Extract/extrait de feuilles), Citric Acid, Maris Limus, Sodium Benzoate, Potassium Sorbate, Ethylhexylglycerin, Natural Fragrance/Fragrance Naturelle (Parfum).

Questions or Comments

Call 1-800-428-1668

Monday-Friday 8 AM MST-5 PM MST

Distributed by
mineral fusion natural brands™
600 West Bayaud Ave.
Denver, CO 80223

PRINCIPAL DISPLAY PANEL - 250 mL Tube Label

MINERAL FUSION®
minerals on a mission®

anti-dandruff
shampoo
CONTROLS THE SYMPTOMS
OF DANDRUFF

Controls flakes
Removes build up
Promotes scalp health

GLUTEN FREE :: CRUELTY FREE :: SULFATE FREE

250 mL / 8.5 fl oz e